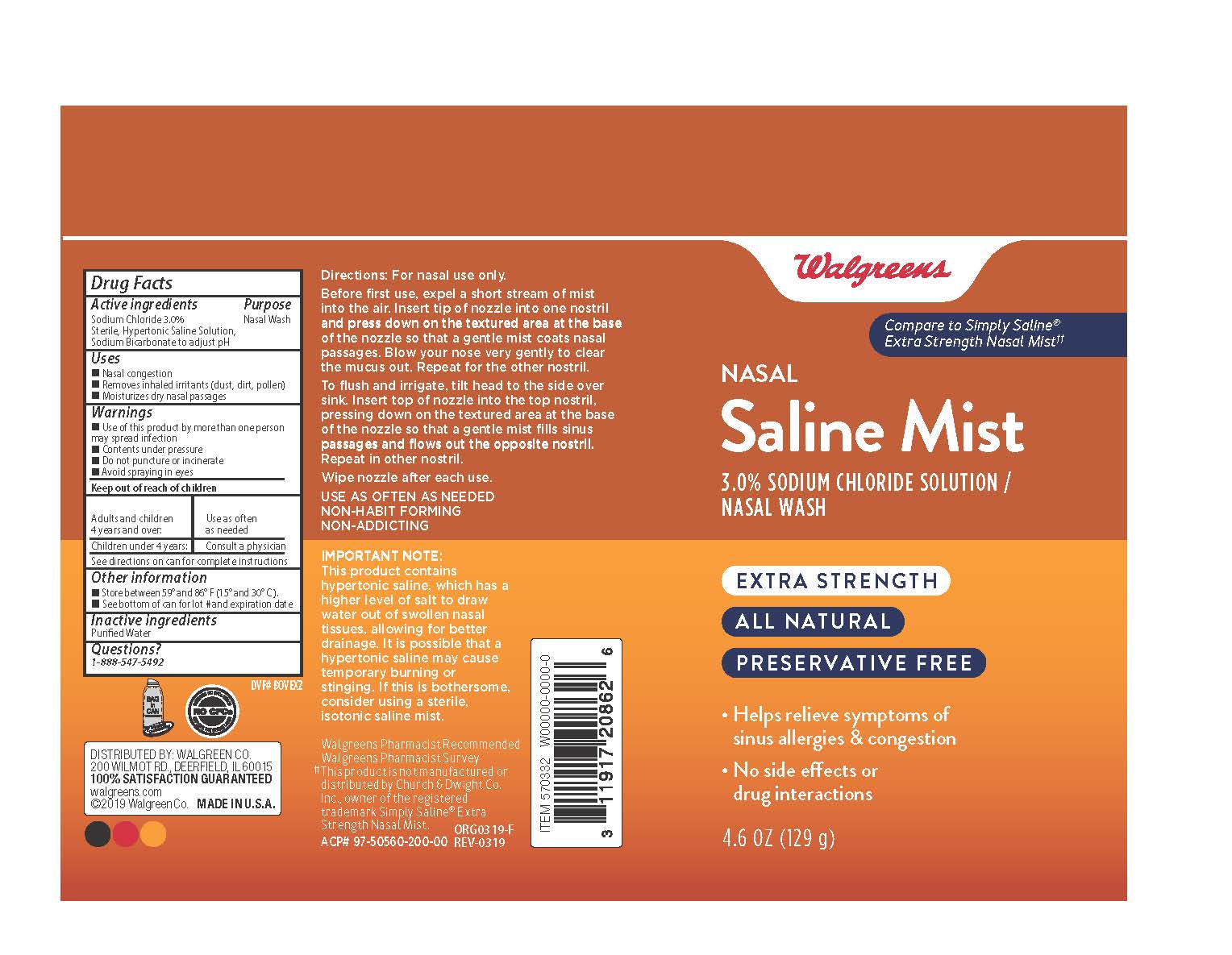 DRUG LABEL: Walgreens Saline Mist

NDC: 0363-1505 | Form: SPRAY
Manufacturer: Walgreen's Corporation
Category: otc | Type: HUMAN OTC DRUG LABEL
Date: 20241218

ACTIVE INGREDIENTS: SODIUM CHLORIDE 3 g/100 g
INACTIVE INGREDIENTS: WATER

Walgreens Extra Strength Nasal Saline Mist

Active Ingredient

Sodium Chloride 3.0%

Sterile, Hypertonic Saline Solution,

Sodium Bicarbonate to adjust pH

Purpose

Nasal Wash

Inactive ingredients

Purfied Water

Uses

- Nasal congestion
- Removes inhaled irritants (dust, dirt, pollen)
- Moisturizes dry nasal passages

Directions

For nasal use only.

Before use, expel a shoet stream of mist into the air. Insert tip of nozzle into one nostril and press down on the textured area at the base of the nozzle so that a gentle mist coats nasal passages. Blow your nose very gently to clear the mucus out. Repeat for the other nostriil.

To flush and irrigate, tilt head to the side over sink. Insert top of nozzle into the top nostril, pressing down on the textured area at the base of the nozzle so that a gentle mist fills sinus passages and flows out the opposite nostril. Repeat in other nostril.

Wipe nozzle after each use.

USE AS OFTEN AS NEEDED

NON-HABIT FORMING

NON-ADDICTING

Warnings

- Use of this product by more than one person may spread infection
- Contents under pressure
- Do not puncture or incinerate
- Avoid spraying in eyes

Keep out of reach of chlidren.

Adults and children 4 years and over: | Use as often as needed
Children under 4 years: | Consult a physician

See directions on can for complere instructions